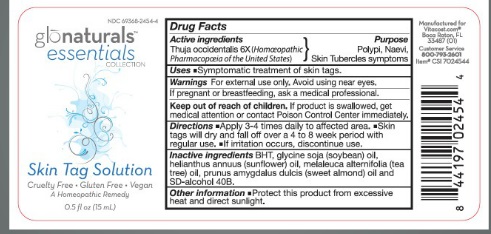 DRUG LABEL: Skin Tag Solution
NDC: 69368-2454 | Form: LIQUID
Manufacturer: VITACOST.COM, INC.
Category: homeopathic | Type: HUMAN OTC DRUG LABEL
Date: 20150630

ACTIVE INGREDIENTS: THUJA OCCIDENTALIS WHOLE 6 [hp_X]/100 mL
INACTIVE INGREDIENTS: BUTYLATED HYDROXYTOLUENE; SOYBEAN OIL; SUNFLOWER OIL; TEA TREE OIL; ALMOND OIL; ALCOHOL

ACTIVE INGREDIENT

THUJUS OFFICINALIS 6X

PURPOSE

POLPI, NAEVI, SKIN TUBERCLES SYMPTOMS

USES

SYMPTOMATIC TREATMENT OF SKIN TAGS

WARNINGS

FOR EXTERNAL USE ONLY. AVOID USING NEAR EYES.

IF PREGNANT OR BREAST FEEDING, ASK A MEDICAL PROFESSIONAL.

DIRECTIONS

- APPLY 3-4 TIMES DAILY TO AFFECTED AREA.
- SKIN TAGS WILL DRY AND FALL OFF OVER A 4 TO 8 WEEK PERIOD WITH REGULAR USE.
- IF IRRITATION OCCURS, DISCONTINUE USE.

OTHER INFORMATION

- PROTECT THIS PRODUCT FROM EXCESSIVE HEAT AND DIRECT SUNLIGHT.

INACTIVE INGREDIENTS

BHT, GLYCINE SOYA (SOYBEAN) OIL, HELIANTHUS ANNUUS (SUNFLOWER) SEED OIL, MELALEUCA ALTERNIFOLIA (TEA TREE) OIL, PRUNUS AMYGDALUS DULCIS (SWEET ALMOND) OIL AND SD-ALCOHOL 40B.